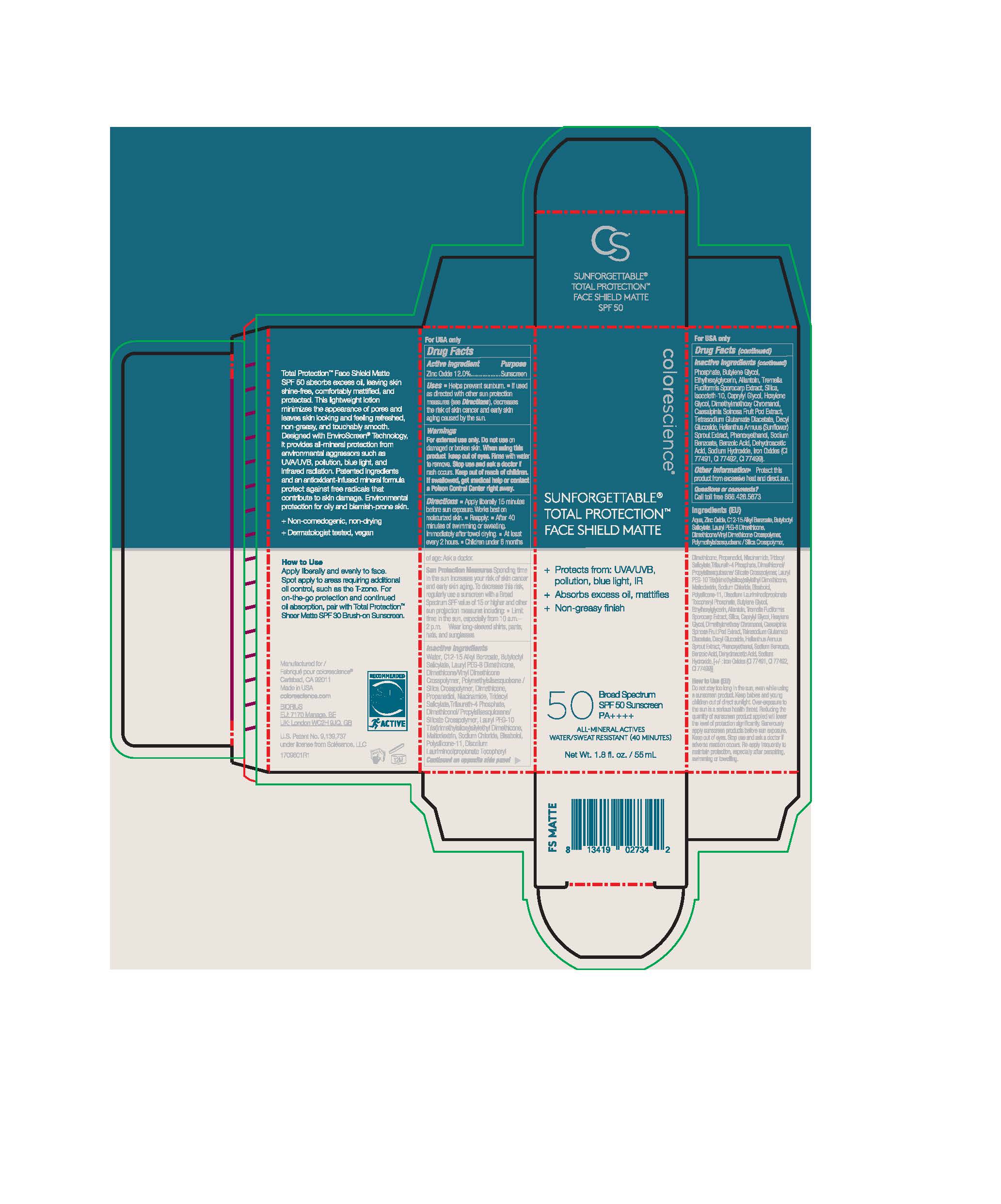 DRUG LABEL: Sunforgettable Total Protection Face Shield Matte
NDC: 68078-038 | Form: LOTION
Manufacturer: Colorescience
Category: otc | Type: HUMAN OTC DRUG LABEL
Date: 20251015

ACTIVE INGREDIENTS: ZINC OXIDE 135.6 mg/1 mL
INACTIVE INGREDIENTS: BUTYLENE GLYCOL; DECYL GLUCOSIDE; HEXYLENE GLYCOL; ALKYL (C12-15) BENZOATE; DISODIUM LAURIMINODIPROPIONATE TOCOPHERYL PHOSPHATES; ISOCETETH-10; CAESALPINIA SPINOSA FRUIT POD; HELIANTHUS ANNUUS SPROUT; TRIDECYL SALICYLATE; DIMETHYLMETHOXY CHROMANOL; ALLANTOIN; .ALPHA.-BISABOLOL, (+)-; SILICON DIOXIDE; DIMETHICONE/VINYL DIMETHICONE CROSSPOLYMER (SOFT PARTICLE); TRILAURETH-4 PHOSPHATE; BUTYLOCTYL SALICYLATE; NIACINAMIDE; SODIUM HYDROXIDE; WATER; DIMETHICONOL/PROPYLSILSESQUIOXANE/SILICATE CROSSPOLYMER (450000000 MW); ETHYLHEXYLGLYCERIN; DEHYDROACETIC ACID; PROPANEDIOL; TETRASODIUM GLUTAMATE DIACETATE; SODIUM CHLORIDE; PHENOXYETHANOL; TREMELLA FUCIFORMIS FRUITING BODY; MALTODEXTRIN; DIMETHICONE

Sunforgettable Total Protection Face Shield Matte